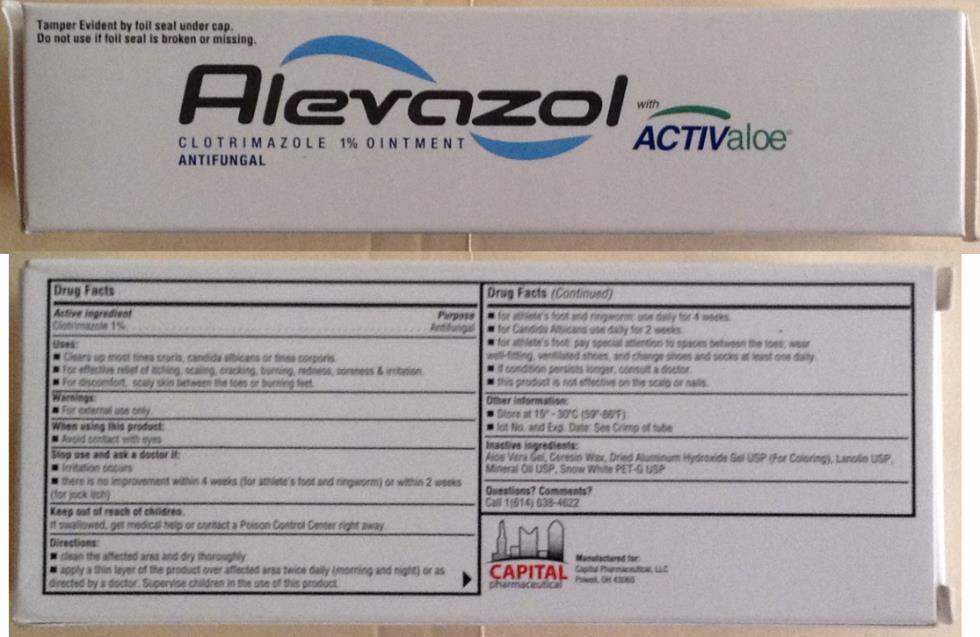 DRUG LABEL: Alevazol
NDC: 29978-918 | Form: OINTMENT
Manufacturer: Capital Pharmaceutical, LLC
Category: otc | Type: HUMAN OTC DRUG LABEL
Date: 20251212

ACTIVE INGREDIENTS: CLOTRIMAZOLE 10 mg/1 g
INACTIVE INGREDIENTS: ALOE VERA WHOLE; CERESIN; ALUMINUM HYDROXIDE; LANOLIN; MINERAL OIL

Alevazol

Alevazol Drug Facts

Active Ingredient

Clotrimazole

Purpose

Antifungal

Uses

- Clears up most tinea cruris, candida albicans or tinea corporis.
- For effective relief of itching, scaling, cracking, burning, redness, soreness & irritation.
- For discomfort, scaly skin between the toes or burning feet.

Warning.

- For external use only.

When Using This Product

- Avoid contact with eyes.

Stop Use and Ask a Doctor if.

- Irritation occurs
- There is no improvement within 4 weeks (for athletes foot and ringworm) or within 2 weeks (for jock itch)

Keep out of reach of children.

- If swallowed get medical help or contact a Poison Control Center right away.

Directions.

- Clean the affected area and dry thoroughly.
- Apply a thin layer of the product over affected area twice daily (morning and night) or as directed by a doctor. Supervise children in the use of this product.
- For athlete’s foot and ringworm: use daily for 4 weeks.
- For Candida Albicans use daily for 2 weeks.
- For athletes foot: Pay special attention to spaces between toes; wear well fitting, ventilated shoes and change shoes and socks at least one daily.
- If condition persists longer, consult a doctor.
- This product is not effective on the scalp or nails

Other Information.

- Store at 15deg –30deg C (59deg-86deg F)
- Lot No and Exp Date: See Crimp of tube.

Inactive Ingredients.

- Aloe Vera Gel, Ceresin Wax, Dried Aluminum Hydroxide Gel USP (for Coloring), Lanolin USP, Mineral Oil USP, Snow White PET-G USP.

Question? Comments?

- Call 1-(614) 638-4622

PRINCIPAL DISPLAY PANEL

Alevazol with ACTIVEaloe®
CLOTRIMAZOLE 1% OINTMENT
ANTIFUNGAL